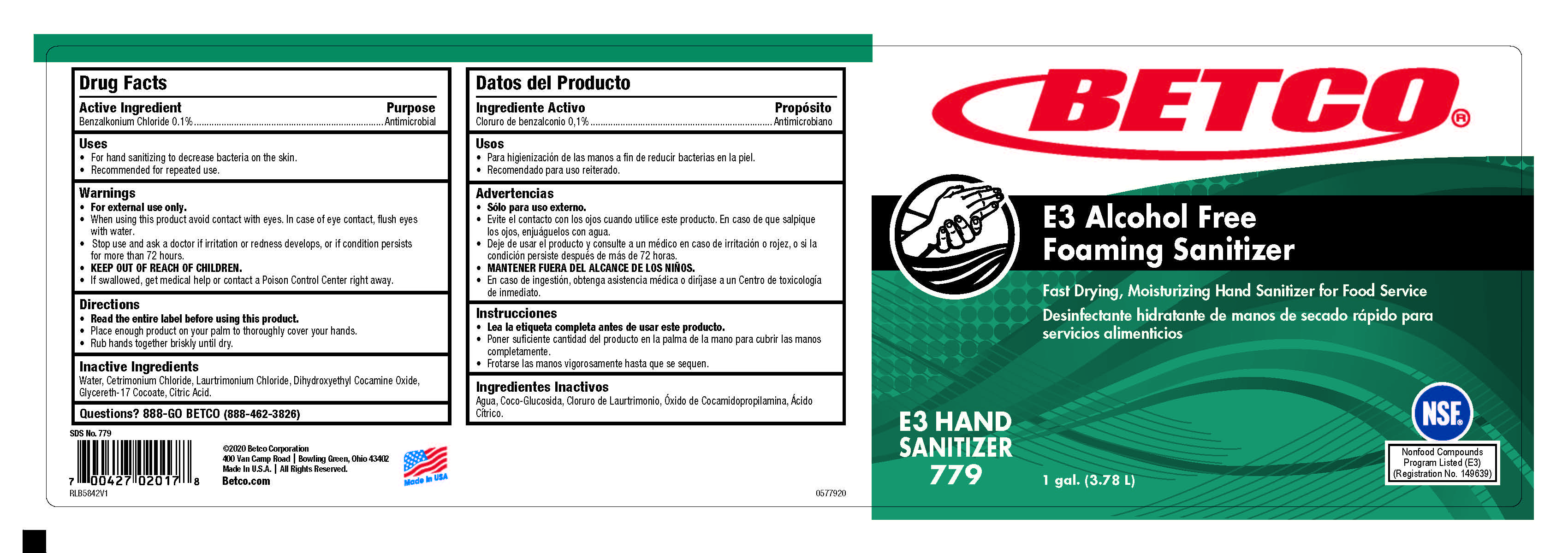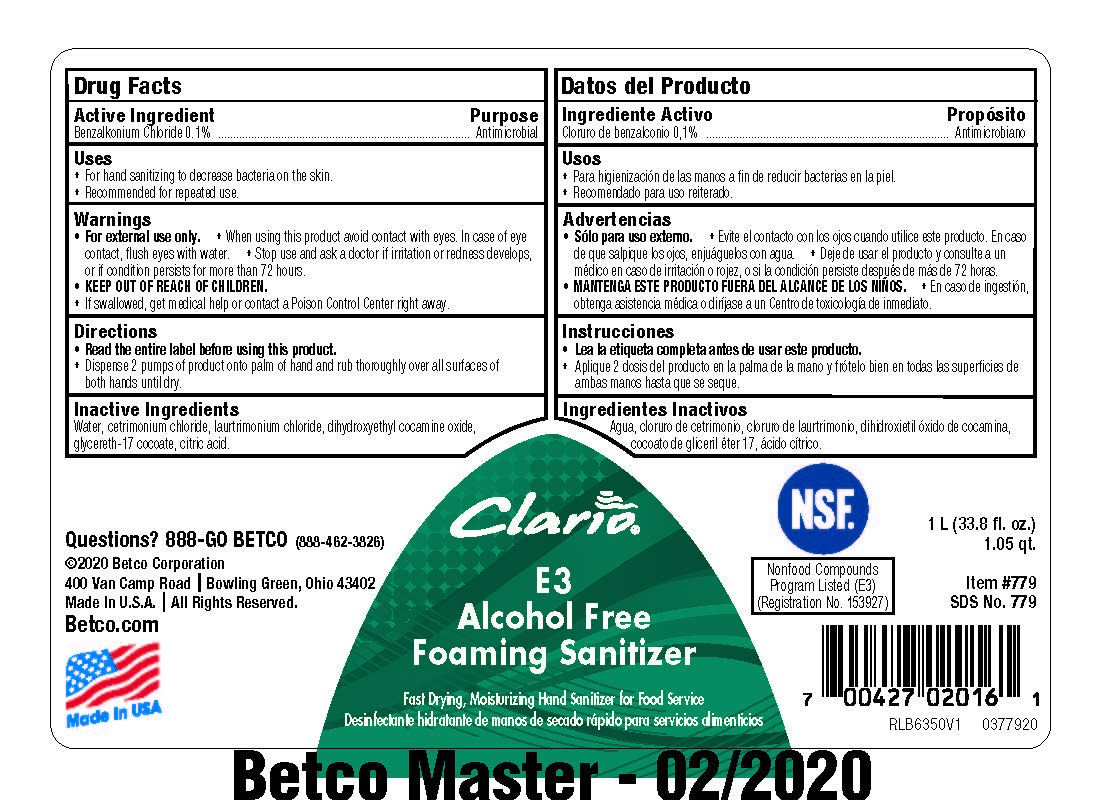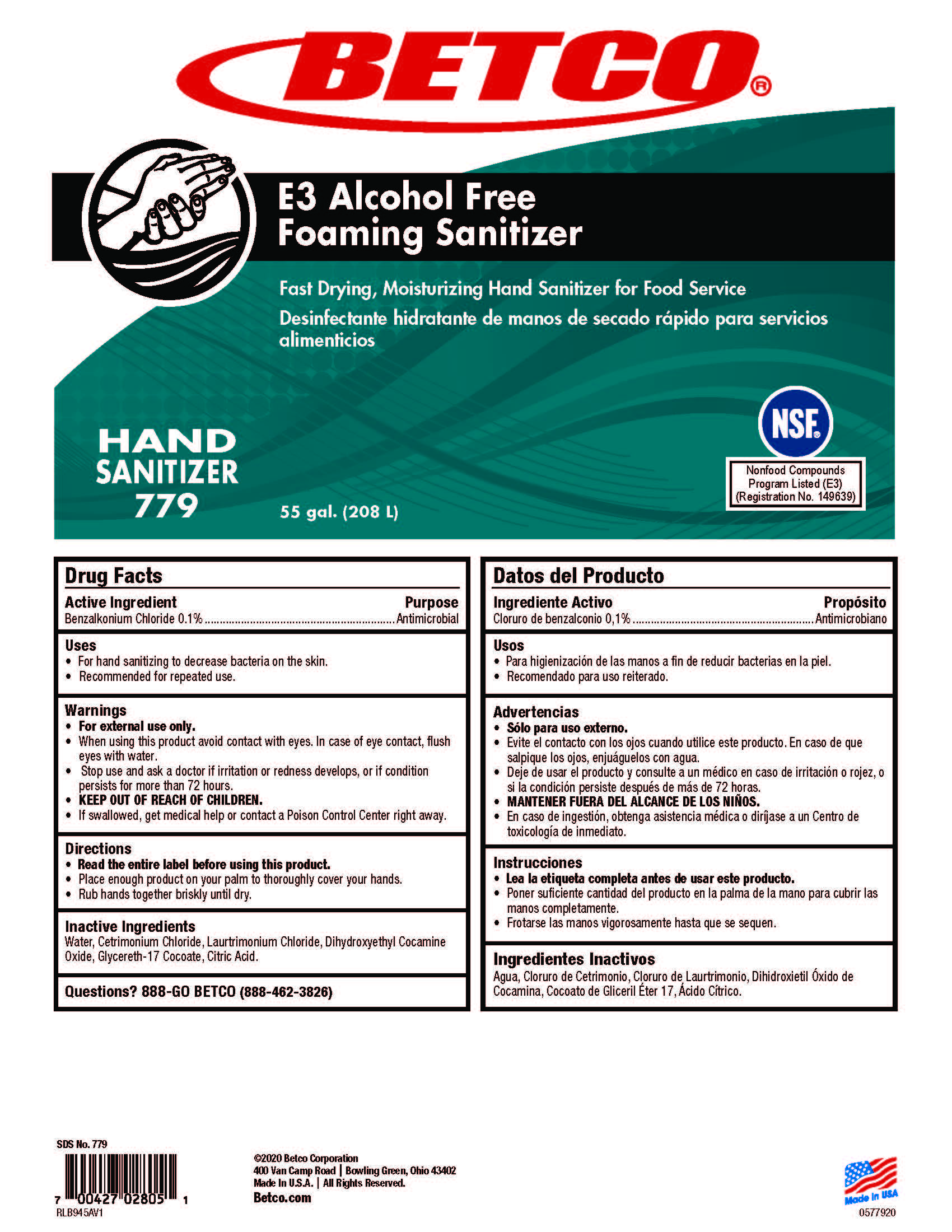 DRUG LABEL: E3 Alcohol Free Foaming Sanitizer
NDC: 65601-779 | Form: SOAP
Manufacturer: Betco Corporation, Ltd.
Category: otc | Type: HUMAN OTC DRUG LABEL
Date: 20240703

ACTIVE INGREDIENTS: BENZALKONIUM CHLORIDE 1 mg/1 mL
INACTIVE INGREDIENTS: WATER; CETRIMONIUM CHLORIDE; LAURTRIMONIUM CHLORIDE; DIHYDROXYETHYL COCAMINE OXIDE

E3 Alcohol Free Foaming Sanitizer